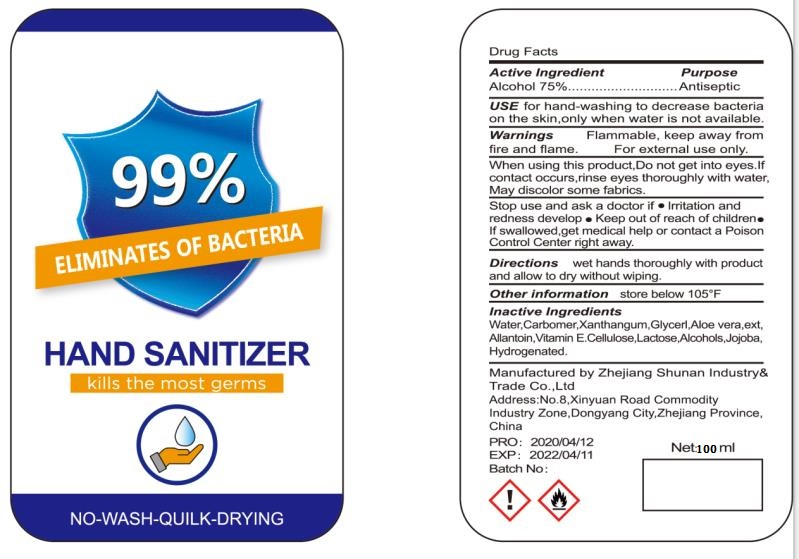 DRUG LABEL: Hand Sanitizer
NDC: 75556-004 | Form: GEL
Manufacturer: ZHEJIANG SHUNAN INDUSTRY&TRADE CO.,LTD
Category: otc | Type: HUMAN OTC DRUG LABEL
Date: 20200519

ACTIVE INGREDIENTS: ALCOHOL 75 mL/100 mL
INACTIVE INGREDIENTS: .ALPHA.-TOCOPHEROL; CARBOMER HOMOPOLYMER, UNSPECIFIED TYPE; WATER; ALOE

DOSAGE AND ADMINISTRATION

store below 105°F

INACTIVE INGREDIENT

Water ，carbomer , Aloe Vera， Vitamin E

INDICATIONS AND USAGE

wet hands thoroughly with product and allow to dry without wiping.

ACTIVE INGREDIENT

Ethanol

keep out of reach of children

PURPOSE

Disinfection
Sterilization
No Rinseing

WARNINGS

Flammable, keep away from fire and flame.